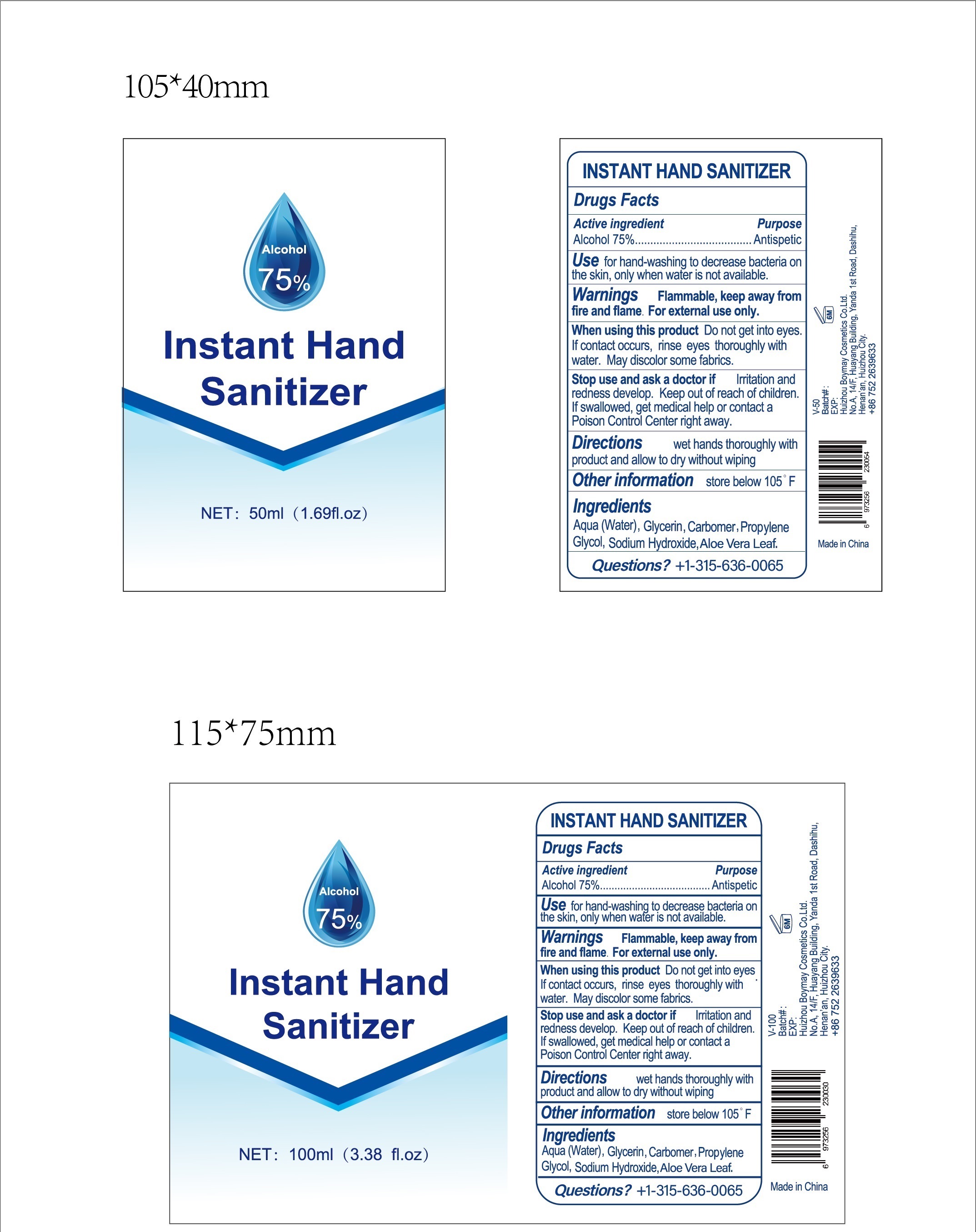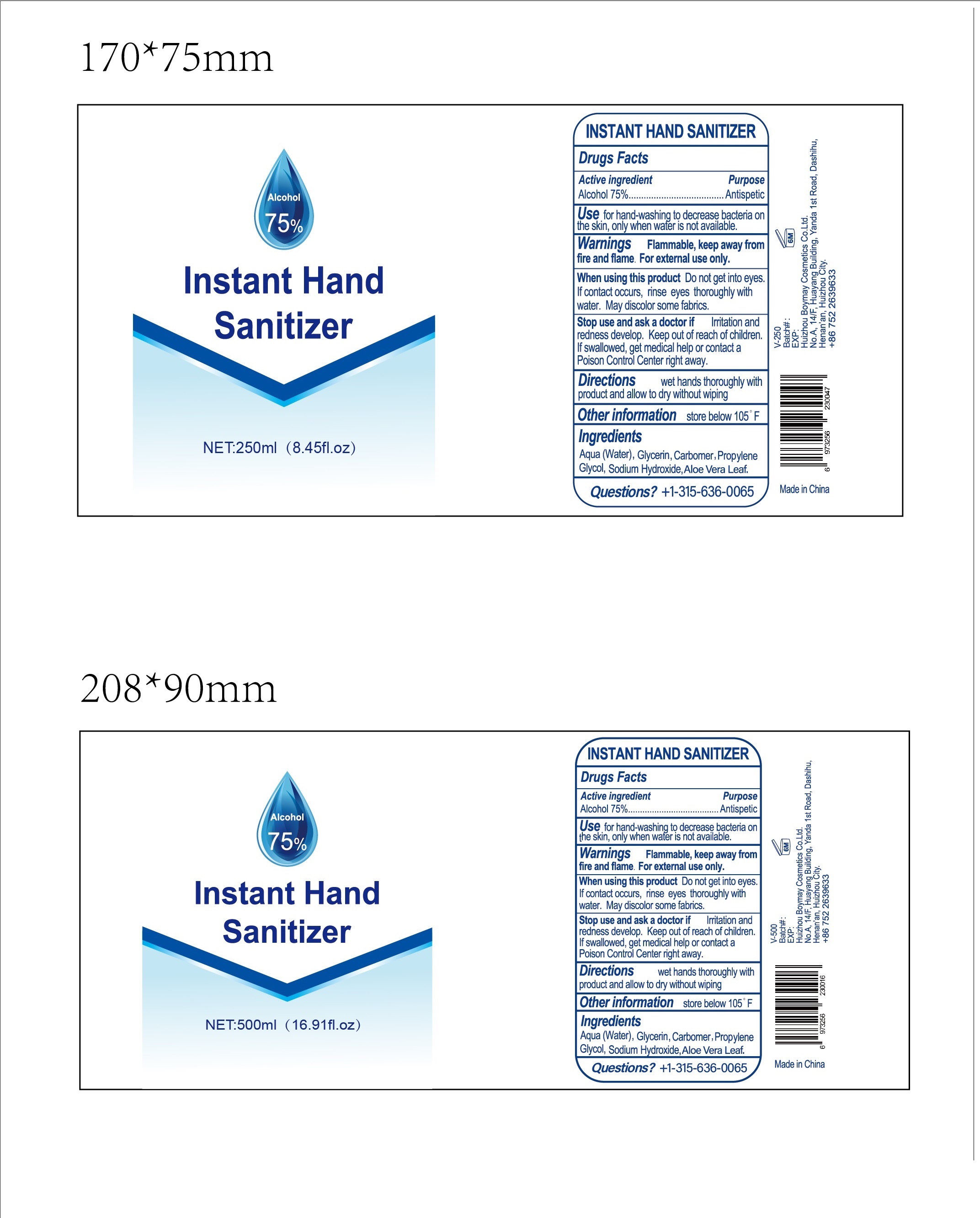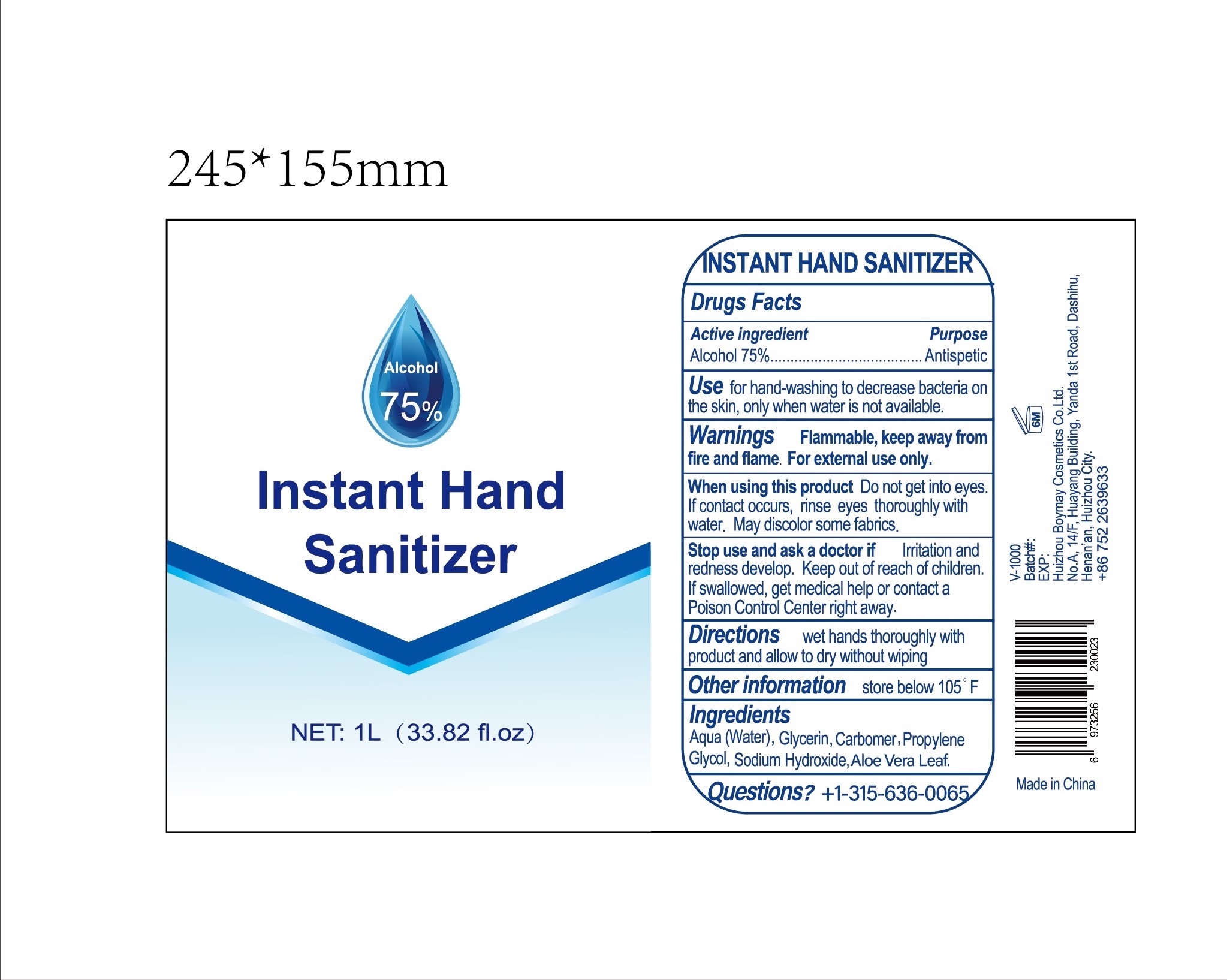 DRUG LABEL: Hand Sanitizer
NDC: 77257-001 | Form: GEL
Manufacturer: Huizhou boymay cosmetics Co. Ltd
Category: otc | Type: HUMAN OTC DRUG LABEL
Date: 20200512

ACTIVE INGREDIENTS: ALCOHOL 75 mL/100 mL
INACTIVE INGREDIENTS: SODIUM HYDROXIDE; CARBOMER 980; ALOE VERA LEAF; PROPYLENE GLYCOL; WATER; GLYCERIN

Boymay Hand sanitizer

ACTIVE INGREDIENT

Alcohol 75%

PURPOSE

Antiseptic

Use

For hand-washing to decrease bacteria on the skin, only when water is not available.

Warnings

Flammable, keep away from fire and flame. For external use only.

When using this product: Do not get into eyes. If contact occurs, rinse eyes thoroughtly with water. May discolor some fabrics.

Stop use and ask a doctor If irritation and redness develop

KEEP OUT OF REACH OF CHILDREN.

ASK DOCTOR

If swallowed, get medical help or contact a Poison Control Center right away.

Directions

Wet hand thoroughly with proudct and allow to dry without wiping.

Other information

Store below 105oF

INACTIVE INGREDIENT

Aqua(Water), Glycerin, Carbomer, Propylene Glycol, Sodium Hydroxide, Aloe Vera Leaf.

QUESTIONS

+1-315-636-0065

PACKAGE LABEL

50ml NDC: 77257-001-11; 100ml NDC: 77257-001-12; 250ml NDC: 77257-001-13, 77257-001-14; 500ml NDC: 77257-001-15; 1000ml NDC: 77257-001-20